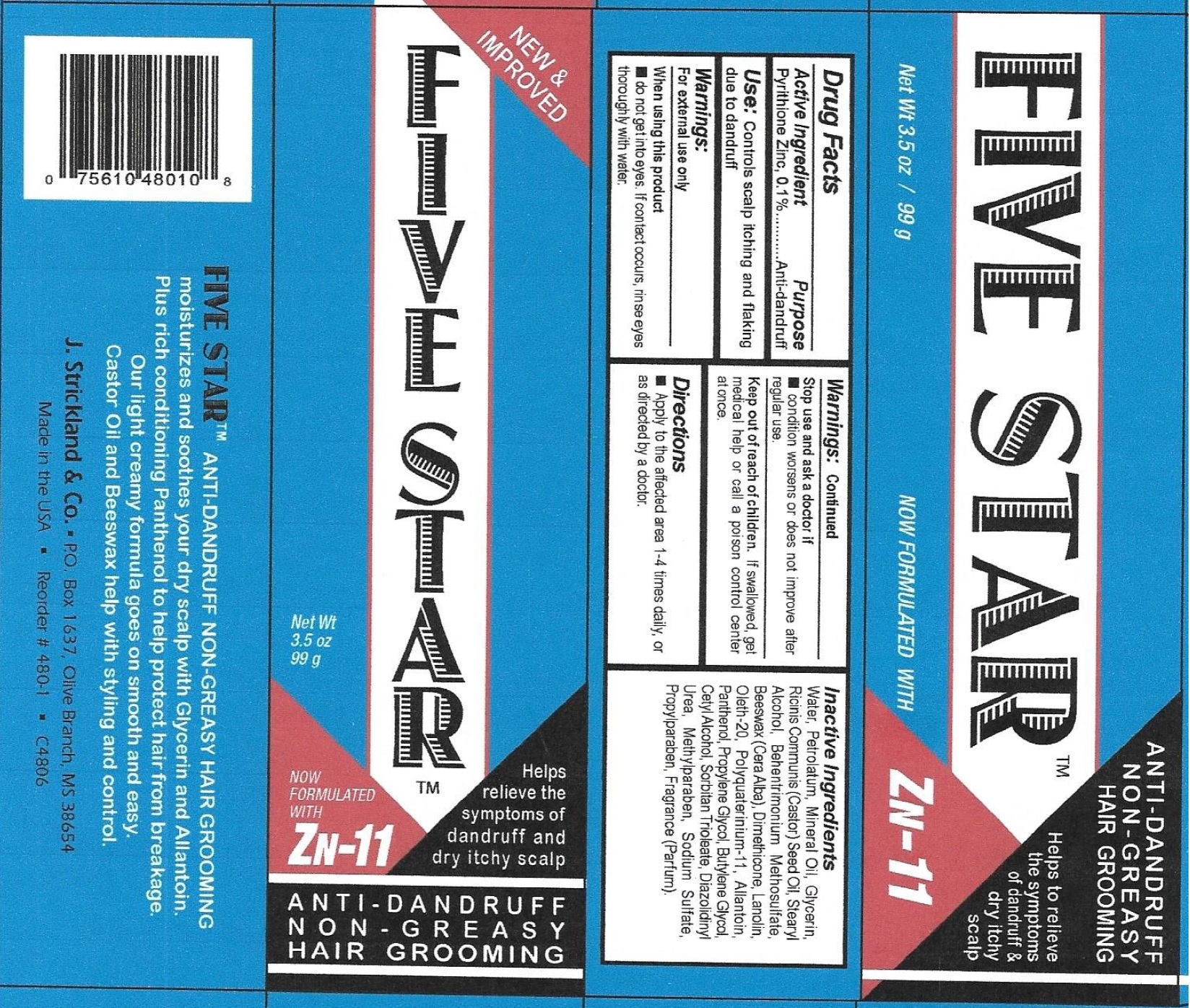 DRUG LABEL: Sulfur 8 Five Star Anti-Dandruff Hair Groom
NDC: 12022-030 | Form: CREAM
Manufacturer: J. Strickland & Co.
Category: otc | Type: HUMAN OTC DRUG LABEL
Date: 20231021

ACTIVE INGREDIENTS: PYRITHIONE ZINC 1 mg/1 g
INACTIVE INGREDIENTS: WATER; PETROLATUM; MINERAL OIL; GLYCERIN; STEARYL ALCOHOL; BEHENTRIMONIUM METHOSULFATE; DIMETHICONE; LANOLIN; OLETH-20; ALLANTOIN; PANTHENOL; PROPYLENE GLYCOL; BUTYLENE GLYCOL; CETYL ALCOHOL; SORBITAN TRIOLEATE; DIAZOLIDINYL UREA; METHYLPARABEN; SODIUM SULFATE; PROPYLPARABEN

Sulfur 8 Five Star Anti-Dandruff Hair Groom Cream

Active Ingredients

Pyrithione Zinc, 0.1%

Purpose

Anti-dandruff

Use:

Controls scalp itching and flaking due to dandruff

Warnings:

For external use only

When using this product

- do not get into eyes. If contact occurs, rinse eyes thoroughly with water.

Stop use and consult a doctor if

- condition worsens or does not improve after regular use.

Keep out of reach of children

If swallowed, get medical helpor call a poison contril center at once.

Directions

- Apply to the affected area 1-4 times daily, or as dircted by a doctor.

Inactive Ingredients

Water, Petrolatum, Mineral Oil, Glycerin, Ricinis Communis (Castor) Seed Oil, Stearyl Alcohol, Behentrimonium Methosulfate, Beeswax (Cera Alba), Dimethicone, Lanolin, Oleth-20, Polyquaterinium-11, Allantoin, Panthenol, Propylene Glycol, Butylene Glycol, Cetyl Alcohol, Sorbitan Trioleate, Diazolidinyl Urea, Methylparaben, Sodium Sulfate, Propylparaben, Fragrance (Parfum).